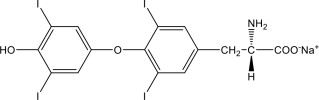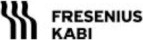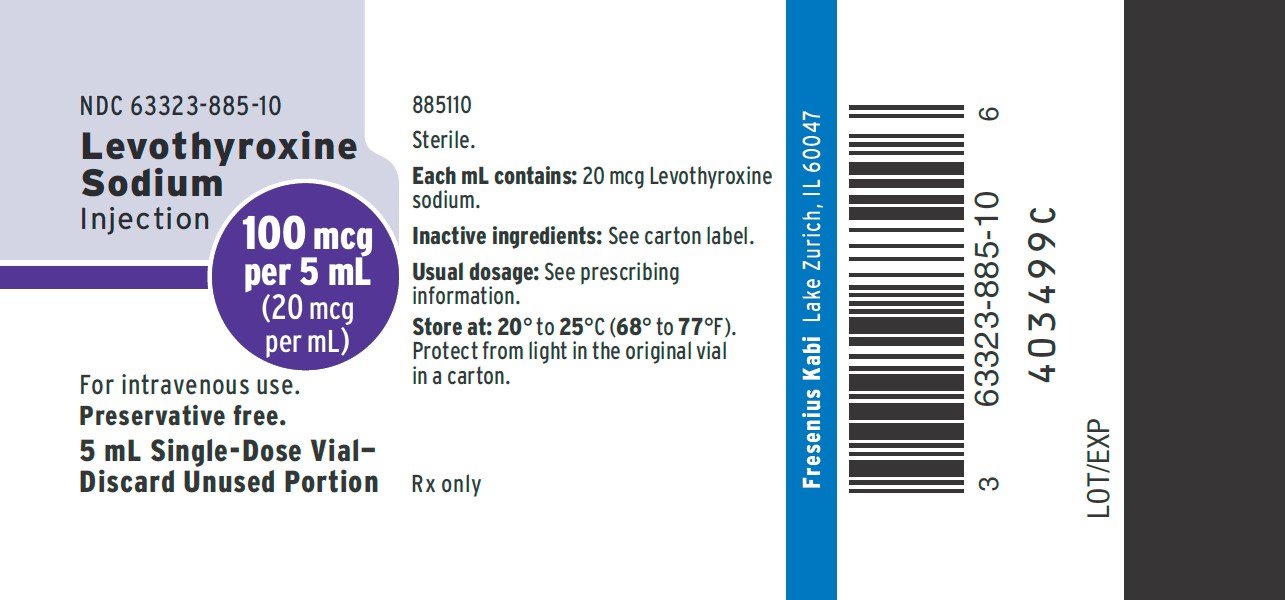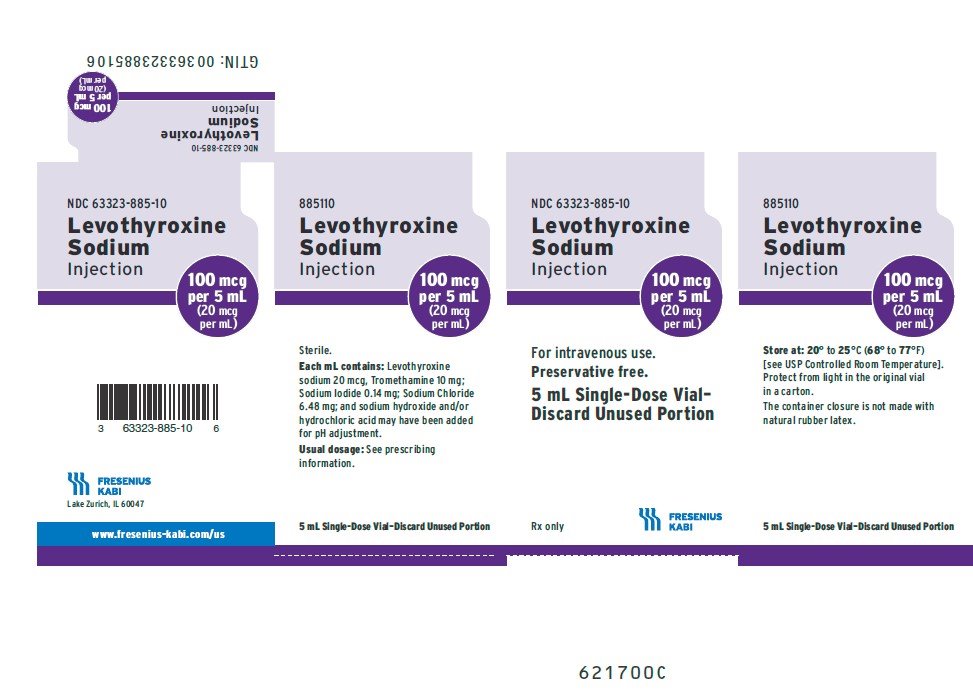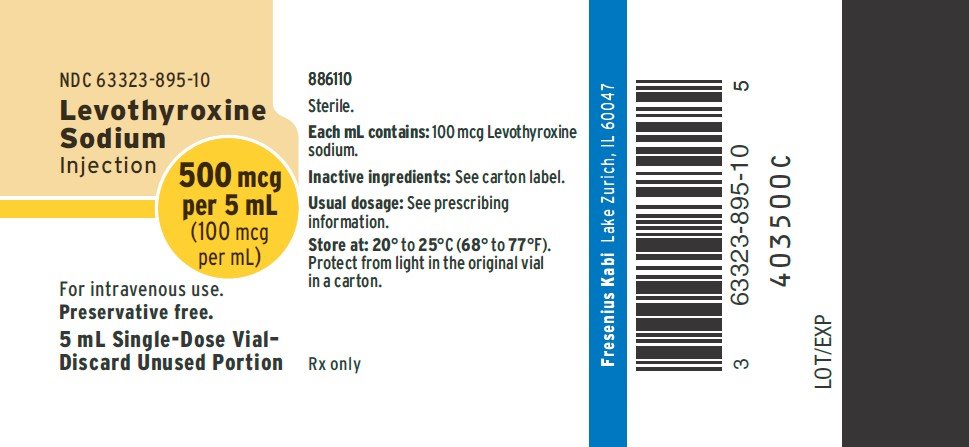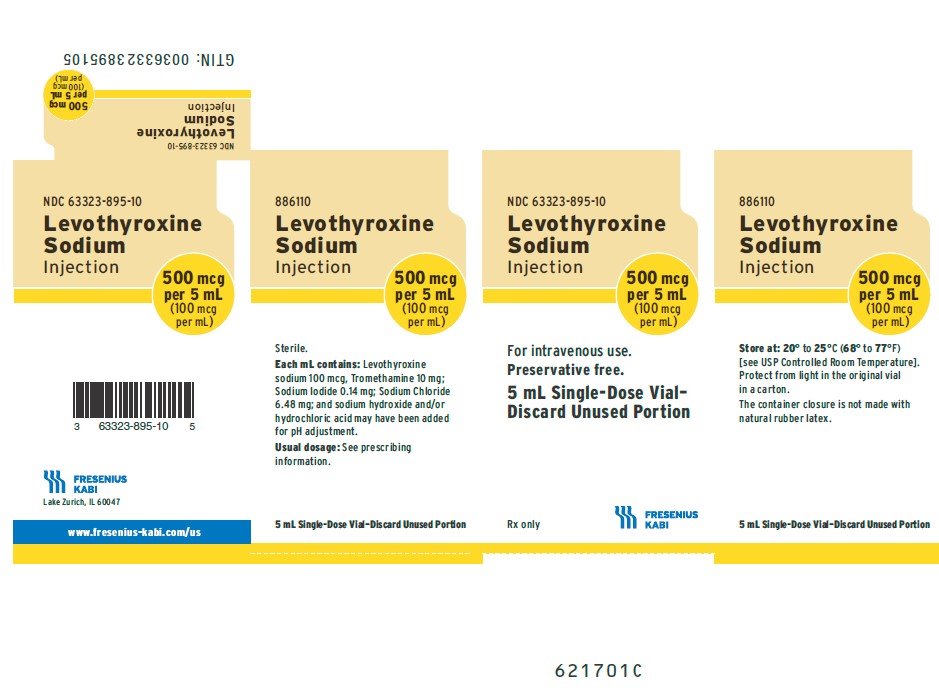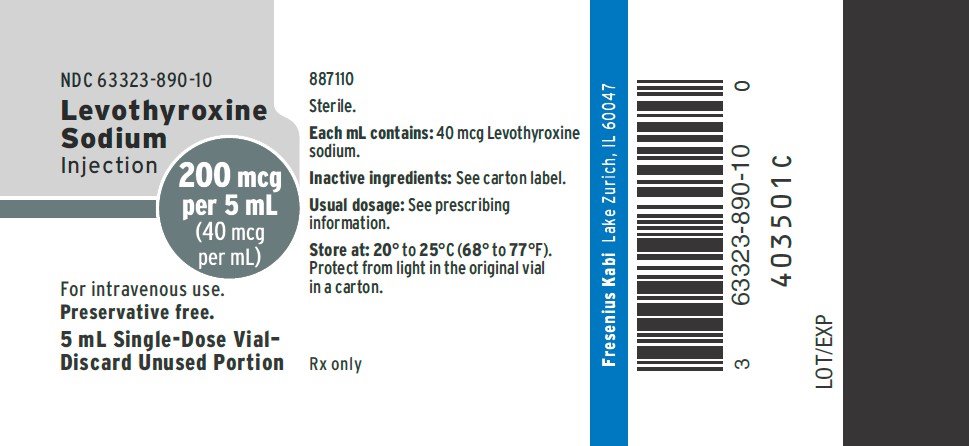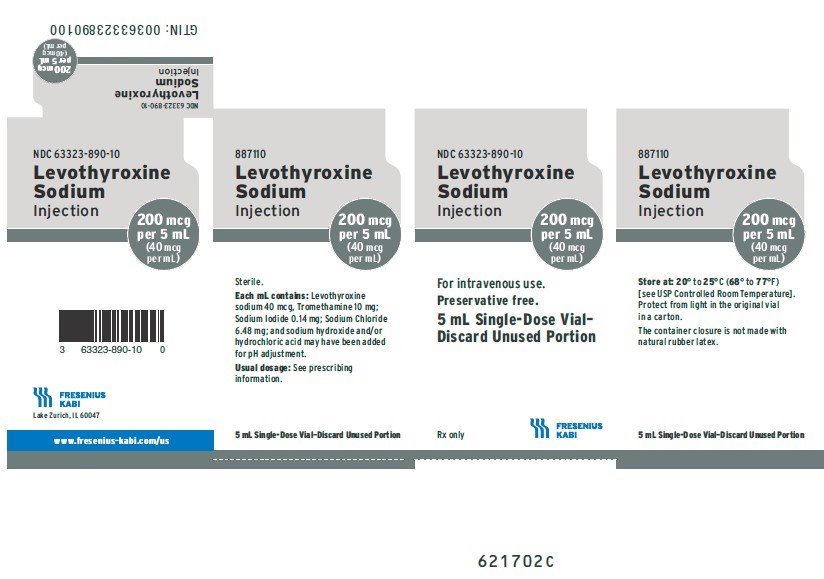 DRUG LABEL: Levothyroxine Sodium
NDC: 63323-885 | Form: INJECTION, SOLUTION
Manufacturer: Fresenius Kabi USA, LLC
Category: prescription | Type: HUMAN PRESCRIPTION DRUG LABEL
Date: 20250317

ACTIVE INGREDIENTS: Levothyroxine sodium 20 ug/1 mL
INACTIVE INGREDIENTS: Tromethamine; Sodium Iodide; Sodium Chloride; Sodium Hydroxide; Hydrochloric Acid

HIGHLIGHTS OF PRESCRIBING INFORMATION

These highlights do not include all the information needed to use LEVOTHYROXINE SODIUM INJECTION safely and effectively.
See full prescribing information for LEVOTHYROXINE SODIUM INJECTION.
LEVOTHYROXINE SODIUM injection, for intravenous use
Initial U.S. Approval: 2002

WARNING: NOT FOR TREATMENT OF OBESITY OR FOR WEIGHT LOSS

Thyroid hormones, including Levothyroxine Sodium Injection, should not be used for the treatment of obesity or for weight loss.

Larger doses may produce serious or even life threatening manifestations of toxicity. (6,10)

1 INDICATIONS AND USAGE

Levothyroxine Sodium Injection is L-thyroxine (T4) indicated in adult patients for the treatment of myxedema coma. (1)

Limitations of Use:

Not recommended as a substitute for oral levothyroxine sodium because the relative bioavailability of Levothyroxine Sodium Injection to oral levothyroxine sodium has not been established and there is a risk of inaccurate dose conversion. (1)

2 DOSAGE AND ADMINISTRATION

- Consider the age, general physical condition, cardiac risk factors, and clinical severity of myxedema and duration of myxedema symptoms when determining dosages of Levothyroxine Sodium Injection. (2.1)
- Start with lower doses in elderly patients and in patients with underlying cardiovascular disease. (2.1)
- The recommended loading dose is 300 mcg to 500 mcg administered intravenously. (2.1)
- The recommended maintenance dose is 50 mcg to 100 mcg administered intravenously daily until the patient can tolerate oral therapy. (2.1)
- Administer Levothyroxine Sodium Injection intravenously at a rate not to exceed 100 mcg per minute. (2.2)
- Do not add Levothyroxine Sodium Injection to intravenous fluids. (2.2)

3 DOSAGE FORMS AND STRENGTHS

Injection:

- 100 mcg per 5 mL (20 mcg per mL) single-dose vial
- 200 mcg per 5 mL (40 mcg per mL) single-dose vial
- 500 mcg per 5 mL (100 mcg per mL) single-dose vial (3)

4 CONTRAINDICATIONS

Uncorrected adrenal insufficiency. (4)

5 WARNINGS AND PRECAUTIONS

- Cardiac Adverse Reactions in the Elderly and in Patients with Underlying Cardiovascular Disease: Overtreatment may cause arrhythmias, tachycardia, myocardial ischemia and infarction, or worsening of congestive heart failure and death, particularly in patients with cardiovascular disease and in elderly patients. Start with lower doses in elderly patients and in patients with underlying cardiovascular disease and monitor patients after administration (5.1).
- Acute Adrenal Crisis in Patients with Concomitant Adrenal Insufficiency: Initiation of thyroid hormone therapy prior to initiating glucocorticoid therapy may precipitate an acute adrenal crisis in patients with adrenal insufficiency. Treat patients with adrenal insufficiency with replacement glucocorticoids prior to initiating treatment (5.2).
- Worsening of Diabetic Control: May worsen glycemic control and result in increased antidiabetic agent or insulin requirements. Carefully monitor glycemic control (5.3).

6 ADVERSE REACTIONS

Adverse reactions associated with Levothyroxine Sodium Injection are primarily those of hyperthyroidism due to therapeutic overdosage: fatigue, increased appetite, weight loss, heat intolerance, fever, excessive sweating, headache, hyperactivity, nervousness, anxiety, irritability, emotional lability, insomnia, tremors, muscle weakness, muscle spasm, palpitations, tachycardia, arrhythmias, increased pulse and blood pressure, heart failure, angina, myocardial infarction, cardiac arrest, dyspnea, diarrhea, vomiting, abdominal cramps, elevations in liver function tests, flushing, and rash. (6)

To report SUSPECTED ADVERSE REACTIONS, contact Fresenius Kabi USA, LLC at 1-800-551-7176 or FDA at 1-800-FDA-1088 or www.fda.gov/medwatch.

7 DRUG INTERACTIONS

See full prescribing information for drugs that affect thyroid hormone pharmacokinetics and metabolism (e.g., synthesis, secretion, catabolism, protein binding, and target tissue response) that may alter the therapeutic response to Levothyroxine Sodium Injection. (7)

FULL PRESCRIBING INFORMATION

WARNING: NOT FOR TREATMENT OF OBESITY OR FOR WEIGHT LOSS

Thyroid hormones, including Levothyroxine Sodium Injection, should not be used for the treatment of obesity or for weight loss.

Larger doses may produce serious or even life threatening manifestations of toxicity. (6,10)

1 INDICATIONS AND USAGE

Levothyroxine Sodium Injection is indicated for the treatment of myxedema coma.

Limitations of Use:

Not recommended as a substitute for oral levothyroxine sodium because the relative bioavailability of Levothyroxine Sodium Injection to oral levothyroxine sodium has not been established and there is a risk of inaccurate dose conversion.

2 DOSAGE AND ADMINISTRATION

2.1 Dosage

- Consider the age, general physical condition, cardiac risk factors, and clinical severity of myxedema and duration of myxedema symptoms when determining the starting and maintenance dosages of Levothyroxine Sodium Injection.
- Start with lower doses in elderly patients and in patients with underlying cardiovascular disease [see Warnings and Precautions (5.1) and Use in Specific Populations (8.5)].
- The recommended loading dose of Levothyroxine Sodium Injection is 300 mcg to 500 mcg administered intravenously.
- The recommended maintenance dose of Levothyroxine Sodium Injection is 50 mcg to 100 mcg administered intravenously daily until the patient can tolerate oral therapy.

2.2 Administration Instructions

- Administer Levothyroxine Sodium Injection as an intravenous injection at a rate not to exceed 100 mcg per minute.
- Do not add Levothyroxine Sodium Injection to intravenous fluids.
- Inspect Levothyroxine Sodium Injection visually prior to injection. It should appear clear and colorless, solution free of visible particulates. Do not use if particulate matter or coloration is seen.
- Discard any unused portion.

3 DOSAGE FORMS AND STRENGTHS

Levothyroxine Sodium Injection is clear, colorless solution supplied as:

- 100 mcg per 5 mL (20 mcg per mL) single-dose vial
- 200 mcg per 5 mL (40 mcg per mL) single-dose vial
- 500 mcg per 5 mL (100 mcg per mL) single-dose vial

4 CONTRAINDICATIONS

Uncorrected adrenal insufficiency [see Warnings and Precautions (5.2)]

5 WARNINGS AND PRECAUTIONS

5.1 Cardiac Adverse Reactions in the Elderly and in Patients with Underlying Cardiovascular Disease

Overtreatment with Levothyroxine Sodium Injection may cause arrhythmias, tachycardia, myocardial ischemia and infarction, or worsening of congestive heart failure and death, particularly in patients with cardiovascular disease and in elderly patients. Start with lower doses in elderly patients and in patients with underlying cardiovascular disease and monitor patients after administration of Levothyroxine Sodium Injection for cardiac adverse reactions.

5.2 Acute Adrenal Crisis in Patients with Concomitant Adrenal Insufficiency

Chronic autoimmune thyroiditis, which can lead to myxedema coma, may occur in association with other autoimmune disorders such as adrenal insufficiency. Thyroid hormone increases metabolic clearance of glucocorticoids. Initiation of thyroid hormone therapy prior to initiating glucocorticoid therapy may precipitate an acute adrenal crisis in patients with adrenal insufficiency [see Contraindications (4)]. Treat patients with adrenal insufficiency with replacement glucocorticoids prior to initiating treatment with Levothyroxine Sodium Injection.

5.3 Worsening of Diabetic Control

Addition of levothyroxine therapy in patients with diabetes mellitus may worsen glycemic control and result in increased antidiabetic agent or insulin requirements. Carefully monitor glycemic control [see Drug Interactions (7.2)].

6 ADVERSE REACTIONS

Adverse reactions associated with levothyroxine are primarily those of hyperthyroidism due to therapeutic overdosage [see Warnings and Precautions (5), Overdosage (10)]. They include the following:

- General: fatigue, increased appetite, weight loss, heat intolerance, fever, excessive sweating
- Central nervous system: headache, hyperactivity, nervousness, anxiety, irritability, emotional lability, insomnia
- Musculoskeletal: tremors, muscle weakness, muscle spasm
- Cardiovascular: palpitations, tachycardia, arrhythmias, increased pulse and blood pressure, heart failure, angina, myocardial infarction, cardiac arrest
- Respiratory: dyspnea
- Gastrointestinal: diarrhea, vomiting, abdominal cramps, elevations in liver function tests
- Dermatologic: flushing, rash

Seizures have been reported rarely with the institution of levothyroxine therapy.

Hypersensitivity Reactions

Hypersensitivity reactions to inactive ingredients have occurred in patients treated with thyroid hormone products. These include urticaria, pruritus, skin rash, flushing, angioedema, various gastrointestinal symptoms (abdominal pain, nausea, vomiting and diarrhea), fever, arthralgia, serum sickness, and wheezing. Hypersensitivity to levothyroxine itself is not known to occur.

7 DRUG INTERACTIONS

7.1 Drugs Known to Affect Thyroid Hormone Pharmacokinetics

Many drugs affect thyroid hormone pharmacokinetics and metabolism (e.g., synthesis, secretion, catabolism, protein binding, and target tissue response) and may alter the therapeutic response to Levothyroxine Sodium Injection (see Tables 1-3).

Table 1: Drugs That May Alter T4 and Triiodothyronine (T3) Serum Transport Without Effecting Free Thyroxine (FT4) Concentration (Euthyroidism)
Drug or Drug Class | Effect
Clofibrate Estrogen-containing oral contraceptives Estrogens (oral) Heroin / Methadone 5-Fluorouracil Mitotane Tamoxifen | These drugs may increase serum thyroxine-binding globulin (TBG) concentration.
Androgens / Anabolic Steroids Asparaginase Glucocorticoids Slow-Release Nicotinic Acid | These drugs may decrease serum TBG concentration.
Potential impact (below): Administration of these agents with levothyroxine results in an initial transient increase in FT4. Continued administration results in a decrease in serum T4 and normal FT4 and TSH concentrations.
Salicylates (> 2 g/day) | Salicylates inhibit binding of T4 and T3 to TBG and transthyretin. An initial increase in serum FT4 is followed by return of FT4 to normal levels with sustained therapeutic serum salicylate concentrations, although total T4 levels may decrease by as much as 30%.
Other drugs: Carbamazepine Furosemide (> 80 mg IV) Heparin Hydantoins Non-Steroidal Anti-inflammatory Drugs - Fenamates | These drugs may cause protein-binding site displacement. Furosemide has been shown to inhibit the protein binding of T4 to TBG and albumin, causing an increase free T4 fraction in serum. Furosemide competes for T4-binding sites on TBG, prealbumin, and albumin, so that a single high dose can acutely lower the total T4 level. Phenytoin and carbamazepine reduce serum protein binding of levothyroxine, and total and free T4 may be reduced by 20% to 40%, but most patients have normal serum TSH levels and are clinically euthyroid. Closely monitor thyroid hormone parameters.

Table 2: Drugs That May Alter Hepatic Metabolism of T4 (Hypothyroidism)
Potential impact: Stimulation of hepatic microsomal drug-metabolizing enzyme activity may cause increased hepatic degradation of levothyroxine, resulting in increased levothyroxine requirements.
Drug or Drug Class | Effect
Phenobarbital Rifampin | Phenobarbital has been shown to reduce the response to thyroxine. Phenobarbital increases L-thyroxine metabolism by inducing uridine 5'-diphospho-glucuronosyltransferase (UGT) and leads to a lower T4 serum levels. Changes in thyroid status may occur if barbiturates are added or withdrawn from patients being treated for hypothyroidism. Rifampin has been shown to accelerate the metabolism of levothyroxine.

Table 3: Drugs That May Decrease Conversion of T4 to T3
Potential impact: Administration of these enzyme inhibitors decreases the peripheral conversion of T4 to T3, leading to decreased T3 levels. However, serum T4 levels are usually normal but may occasionally be slightly increased.
Drug or Drug Class | Effect
Beta-adrenergic antagonists (e.g., Propranolol > 160 mg/day) | In patients treated with large doses of propranolol (> 160 mg/day), T3 and T4 levels change slightly, TSH levels remain normal, and patients are clinically euthyroid. It should be noted that actions of particular beta-adrenergic antagonists may be impaired when the hypothyroid patient is converted to the euthyroid state.
Glucocorticoids (e.g., Dexamethasone ≥ 4 mg/day) | Short-term administration of large doses of glucocorticoids may decrease serum T3 concentrations by 30% with minimal change in serum T4 levels. However, long-term glucocorticoid therapy may result in slightly decreased T3 and T4 levels due to decreased TBG production (See above).
Other drugs: Amiodarone | Amiodarone inhibits peripheral conversion of levothyroxine (T4) to triiodothyronine (T3) and may cause isolated biochemical changes (increase in serum free-T4, and decreased or normal free-T3) in clinically euthyroid patients.

7.2 Antidiabetic Therapy

Addition of levothyroxine to antidiabetic or insulin therapy may result in increased antidiabetic agent or insulin requirements. Careful monitoring of glycemic control is recommended.

7.3 Oral Anticoagulants

Levothyroxine increases the response to oral anticoagulant therapy. Therefore, a decrease in the dose of anticoagulant may be warranted with correction of the hypothyroid state. Closely monitor coagulation tests to permit appropriate and timely dosage adjustments.

7.4 Digitalis Glycosides

Levothyroxine may reduce the therapeutic effects of digitalis glycosides. Serum digitalis glycoside levels may be decreased when a hypothyroid patient becomes euthyroid, necessitating an increase in the dose of digitalis glycosides.

7.5 Antidepressant Therapy

Concurrent use of tricyclic (e.g., amitriptyline) or tetracyclic (e.g., maprotiline) antidepressants and levothyroxine may increase the therapeutic and toxic effects of both drugs, possibly due to increased receptor sensitivity to catecholamines. Toxic effects may include increased risk of cardiac arrhythmias and central nervous system stimulation. Levothyroxine may accelerate the onset of action of tricyclics. Administration of sertraline in patients stabilized on levothyroxine may result in increased levothyroxine requirements.

7.6 Ketamine

Concurrent use of ketamine and levothyroxine may produce marked hypertension and tachycardia. Closely monitor blood pressure and heart rate in these patients.

7.7 Sympathomimetics

Concurrent use may of sympathomimetics and levothyroxine may increase the effects of sympathomimetics or thyroid hormone. Thyroid hormones may increase the risk of coronary insufficiency when sympathomimetic agents are administered to patients with coronary artery disease.

7.8 Drug-Laboratory Test Interactions

Consider changes in TBG concentration when interpreting T4 and T3 values. Measure and evaluate unbound (free) hormone and/or determine the free T4 index (FT4I) in this circumstance. Pregnancy, infectious hepatitis, estrogens, estrogen containing oral contraceptives, and acute intermittent porphyria increase TBG concentrations. Nephrosis, severe hypoproteinemia, severe liver disease, acromegaly, androgens, and corticosteroids decrease TBG concentration. Familial hyper- or hypo-thyroxine binding globulinemias have been described, with the incidence of TBG deficiency approximating 1 in 9,000.

8 USE IN SPECIFIC POPULATIONS

8.1 Pregnancy

Risk Summary

There is no available data with use of Levothyroxine Sodium Injection in pregnant women. The clinical data in pregnant women treated with oral levothyroxine to maintain a euthyroid state have not reported increased rates of major birth defects, miscarriages, or adverse maternal or fetal outcomes (see Data). There are risks to the mother and fetus associated with myxedema coma in pregnancy (see Clinical Considerations). Animal reproduction studies have not been conducted with levothyroxine sodium.

The estimated background risk of major birth defects and miscarriage for the indicated population is unknown. In the U.S. general population, the estimated background risk of major birth defects and miscarriage in clinically recognized pregnancies is 2 to 4% and 15 to 20%, respectively.

Clinical Considerations

Disease-Associated Maternal and/or Embryo/Fetal Risk

Myxedema coma is a medical emergency which can be fatal, if left untreated. Delaying treatment in pregnant women with myxedema coma increases the risk of maternal and fetal morbidity and mortality. Life-sustaining therapy for the pregnant woman should not be withheld due to potential concerns regarding the effects of Levothyroxine Sodium Injection on the fetus.

Data

Human Data

There is no available data with use of Levothyroxine Sodium Injection in pregnant women. Oral levothyroxine is approved for use as a replacement therapy in hypothyroidism. There is a long experience of oral levothyroxine use in pregnant women that has not reported increased rates of fetal malformations, miscarriages or other adverse maternal or fetal outcomes associated with levothyroxine use in pregnant women.

8.2 Lactation

Risk Summary

Published studies report that levothyroxine is present in human milk following the administration of oral levothyroxine. However, there is insufficient information to determine the effects of levothyroxine on the breastfed infant and no available information on the effects of levothyroxine on milk production. There is no available data with use of Levothyroxine Sodium Injection in lactating women. The developmental and health benefits of breastfeeding should be considered along with the mother's clinical need for levothyroxine and any potential adverse effects on the breastfed infant from levothyroxine or from the underlying maternal condition.

8.4 Pediatric Use

The safety and efficacy of Levothyroxine Sodium Injection have not been established in pediatric patients.

8.5 Geriatric Use

Because of the increased prevalence of cardiovascular disease among the elderly, initiate Levothyroxine Sodium Injection with lower doses in elderly patients and in patients with underlying cardiovascular disease and closely monitor for cardiac adverse reactions. Atrial arrhythmias can occur in elderly patients. Atrial fibrillation is the most common of the arrhythmias observed with levothyroxine overtreatment in the elderly [see Dosage and Administration (2.1) and Warnings and Precautions (5.1)].

10 OVERDOSAGE

The signs and symptoms of overdosage are those of hyperthyroidism [see Warnings and Precautions (5) and Adverse Reactions (6)]. In addition, confusion and disorientation may occur. Cerebral embolism, shock, coma, and death have been reported. Reduce the Levothyroxine Sodium Injection dose or temporarily discontinue if signs or symptoms of overdosage occur. Initiate appropriate supportive treatment as dictated by the patient's medical status.

11 DESCRIPTION

Levothyroxine Sodium Injection contains synthetic crystalline levothyroxine (T4) in sodium salt form. Levothyroxine sodium has an empirical formula of C15H10I4NNaO4, a molecular weight of 798.85 g/mol (anhydrous), and the following structural formula:

Levothyroxine Sodium Injection is a sterile, preservative free, clear, colorless, sterile solution for intravenous administration available as: 100 mcg per 5 mL (20 mcg per mL), 200 mcg per 5 mL (40 mcg per mL), and 500 mcg per 5 mL (100 mcg per mL). Each mL of Levothyroxine Sodium Injection also contains 10 mg Tromethamine, USP; 0.14 mg Sodium Iodide, USP; 6.48 mg Sodium Chloride, USP; and Water for Injection, USP Sodium hydroxide, NF and/or Hydrochloric acid, USP may have been added for pH adjustment (9.5 – 10.8). Levothyroxine Sodium Injection is in single dose clear glass vials.

12 CLINICAL PHARMACOLOGY

12.1 Mechanism of Action

Thyroid hormones exert their physiologic actions through control of DNA transcription and protein synthesis. Triiodothyronine (T3) and levothyroxine (T4) diffuse into the cell nucleus and bind to thyroid receptor proteins attached to DNA. This hormone nuclear receptor complex activates gene transcription and synthesis of messenger RNA and cytoplasmic proteins.

The physiological actions of thyroid hormones are produced predominantly by T3, the majority of which (approximately 80%) is derived from T4 by deiodination in peripheral tissues.

12.2 Pharmacodynamics

Levothyroxine sodium is a synthetic T4 hormone that exerts the same physiologic effect as endogenous T4, thereby maintaining normal T4 levels when a deficiency is present.

12.3 Pharmacokinetics

Distribution

Circulating thyroid hormones are greater than 99% bound to plasma proteins, including thyroxine binding globulin (TBG), thyroxine binding prealbumin (TBPA), and albumin (TBA), whose capacities and affinities vary for each hormone. The higher affinity of both TBG and TBPA for T4 partially explains the higher serum levels, slower metabolic clearance, and longer half life of T4 compared to T3. Protein bound thyroid hormones exist in reverse equilibrium with small amounts of free hormone. Only unbound hormone is metabolically active. Many drugs and physiologic conditions affect the binding of thyroid hormones to serum proteins [see Drug Interactions (7)]. Thyroid hormones do not readily cross the placental barrier [see Use in Specific Populations (8.1)].

Metabolism

T4 is slowly eliminated. The major pathway of thyroid hormone metabolism is through sequential deiodination. Approximately eighty percent of circulating T3 is derived from peripheral T4 by monodeiodination. The liver is the major site of degradation for both T4 and T3, with T4 deiodination also occurring at a number of additional sites, including the kidney and other tissues. Approximately 80% of the daily dose of T4 is deiodinated to yield equal amounts of T3 and reverse T3 (rT3). T3 and rT3 are further deiodinated to diiodothyronine. Thyroid hormones are also metabolized via conjugation with glucuronides and sulfates and excreted directly into the bile and gut where they undergo enterohepatic recirculation.

Excretion

Thyroid hormones are primarily eliminated by the kidneys. A portion of the conjugated hormone reaches the colon unchanged, where it is hydrolyzed and eliminated in feces as the free hormones. Urinary excretion of T4 decreases with age.

Table 1: Pharmacokinetic Parameters of Thyroid Hormones in Euthyroid Patients
Hormone | Ratio in Thyroglobulin | Biologic Potency | Half-Life (Days) | Protein Binding (%)^2
T4 | 10 to 20 | 1 | 6 to 8^1 | 99.96
T3 | 1 | 4 | ≤ 2 | 99.5
T4: Levothyroxine
T3: Liothyronine
^1 3 to 4 days in hyperthyroidism, 9 to 10 days in hypothyroidism.
^2 Includes TBG, TBPA, and TBA.

13 NONCLINICAL TOXICOLOGY

13.1 Carcinogenesis, Mutagenesis, Impairment of Fertility

Animal studies have not been performed to evaluate the carcinogenic potential, mutagenic potential or effects on fertility of Levothyroxine Sodium Injection.

16 HOW SUPPLIED/STORAGE AND HANDLING

Levothyroxine Sodium Injection is a clear, colorless solution available as follows:

Product Code | Unit of Sale | Strength | Each
885110 | NDC 63323-885-10; Individually Packaged | 100 mcg per 5 mL; (20 mcg per mL) | NDC 63323-885-10; 5 mL; Single-Dose Vial
886110 | NDC 63323-895-10; Individually Packaged | 500 mcg per 5 mL; (100 mcg per mL) | NDC 63323-895-10; 5 mL; Single-Dose Vial
887110 | NDC 63323-890-10; Individually Packaged | 200 mcg per 5 mL; (40 mcg per mL) | NDC 63323-890-10; 5 mL; Single-Dose Vial

Protect from light in the original vial in a carton and store at 20° to 25°C (68° to 77°F) [see USP Controlled Room Temperature]. The unopened vial may be stored for up to 24 hours exposed to indoor lighting outside of the carton. The drug product is preservative free. Discard any unused portion.

Lake Zurich, IL 60047

www.fresenius-kabi.com/us

451617A

Revised: November 2024

PACKAGE LABEL

PACKAGE LABEL - PRINCIPAL DISPLAY – Levothyroxine Sodium Injection 5 mL Vial Label
NDC 63323-885-10
Levothyroxine Sodium

Injection
100 mcg per 5 mL

(20 mcg per mL)
For intravenous use.

Preservative free.

5 mL Single-Dose Vial-

Discard Unused Portion

PACKAGE LABEL

PACKAGE LABEL - PRINCIPAL DISPLAY – Levothyroxine Sodium Injection 5 mL Carton Panel
NDC 63323-885-10
Levothyroxine Sodium

Injection
100 mcg per 5 mL

(20 mcg per mL)
For intravenous use.

Preservative free.

5 mL Single-Dose Vial-

Discard Unused Portion

Rx only

PACKAGE LABEL

PACKAGE LABEL - PRINCIPAL DISPLAY – Levothyroxine Sodium Injection 5 mL Vial Label
NDC 63323-895-10
Levothyroxine Sodium

Injection
500 mcg per 5 mL

(100 mcg per mL)
For intravenous use.

Preservative free.

5 mL Single-Dose Vial-

Discard Unused Portion

PACKAGE LABEL

PACKAGE LABEL - PRINCIPAL DISPLAY – Levothyroxine Sodium Injection 5 mL Carton Panel
NDC 63323-895-10
Levothyroxine Sodium

Injection
500 mcg per 5 mL

(100 mcg per mL)
For intravenous use.

Preservative free.

5 mL Single-Dose Vial-
Discard Unused Portion

Rx only

PACKAGE LABEL

PACKAGE LABEL - PRINCIPAL DISPLAY – Levothyroxine Sodium Injection 5 mL Vial Label
NDC 63323-890-10
Levothyroxine Sodium

Injection
200 mcg per 5 mL

(40 mcg per mL)
For intravenous use.

Preservative free.

5 mL Single-Dose Vial-

Discard Unused Portion

PACKAGE LABEL

PACKAGE LABEL - PRINCIPAL DISPLAY – Levothyroxine Sodium Injection 5 mL Carton Panel
NDC 63323-890-10
Levothyroxine Sodium

Injection
200 mcg per 5 mL

(40 mcg per mL)
For intravenous use.

Preservative free.

5 mL Single-Dose Vial-

Discard Unused Portion

Rx only